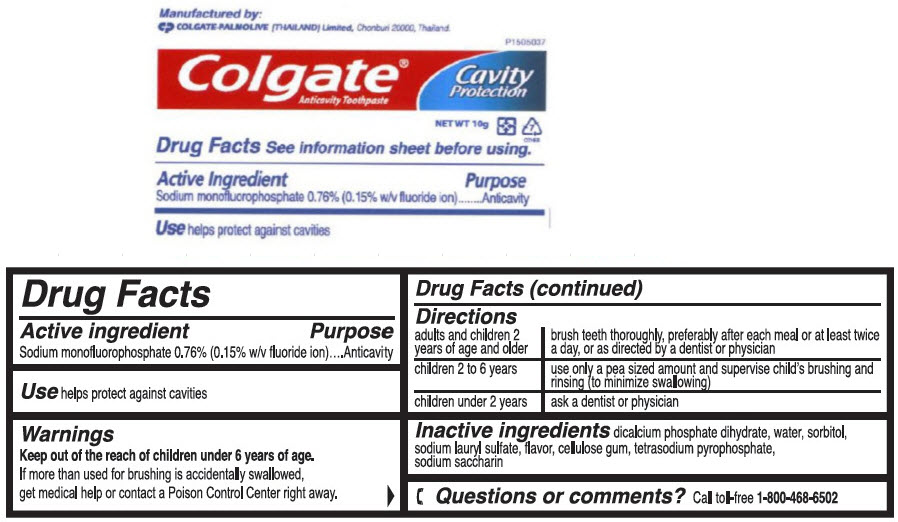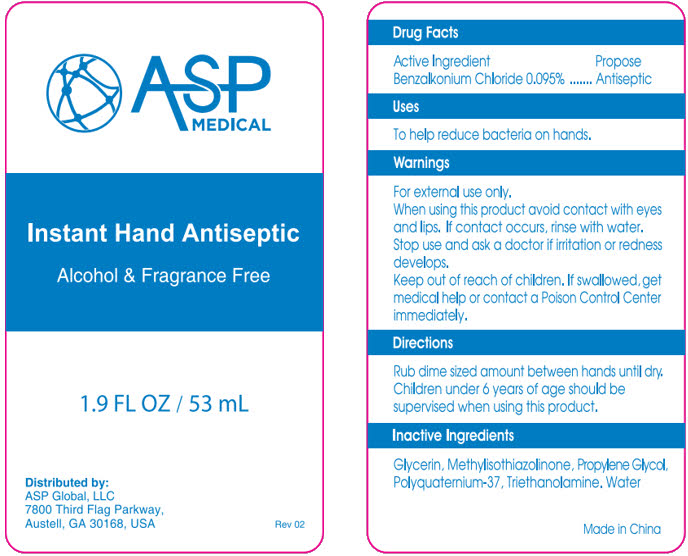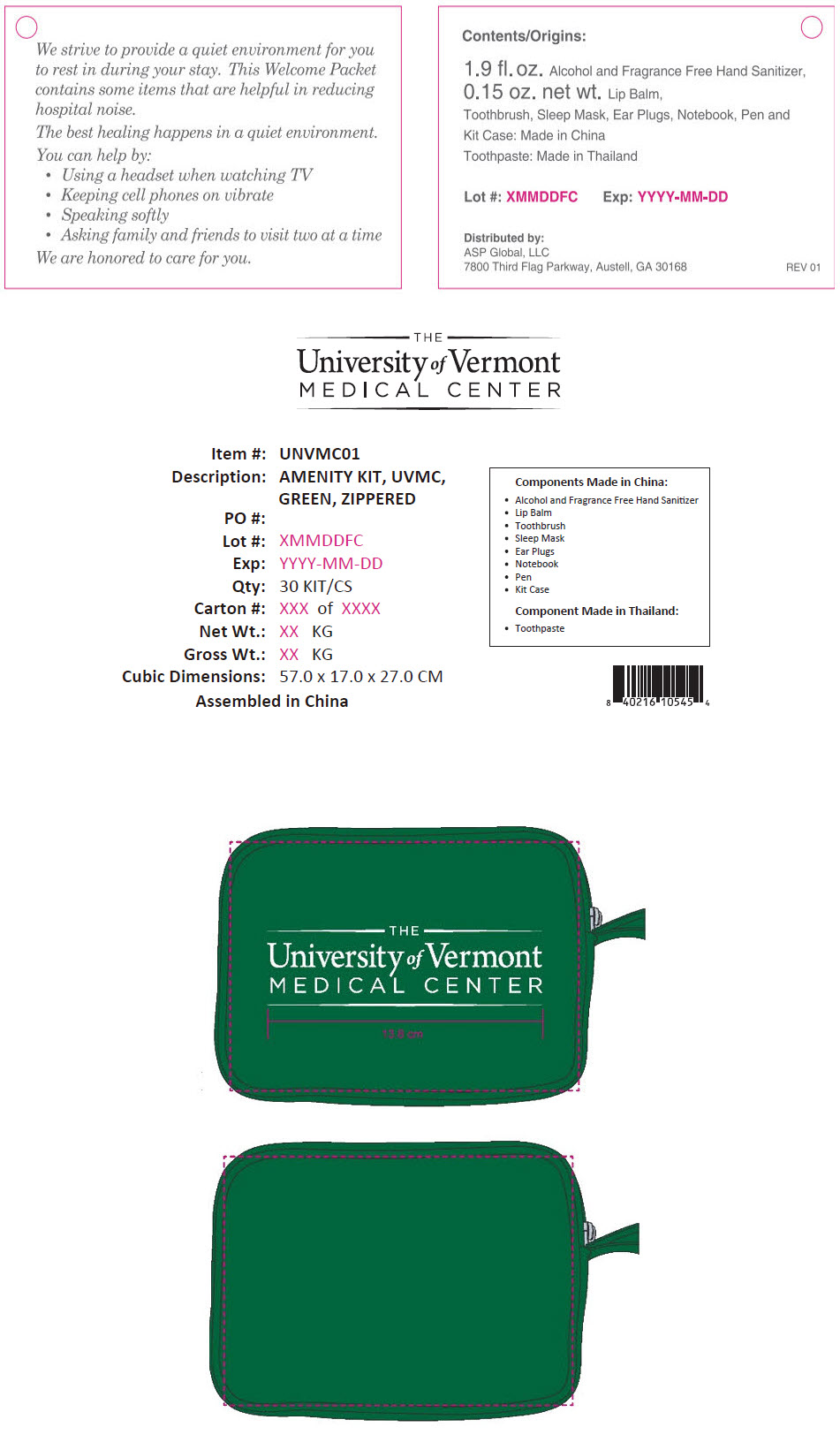 DRUG LABEL: Univ of Vermont Medical Center Amenity
NDC: 59448-500 | Form: KIT | Route: TOPICAL
Manufacturer: ASP Global, LLc
Category: otc | Type: HUMAN OTC DRUG LABEL
Date: 20241217

ACTIVE INGREDIENTS: Benzalkonium Chloride 0.095 mg/100 mL; Sodium Monofluorophosphate 7.6 mg/1 g
INACTIVE INGREDIENTS: Water; Polyquaternium-37 (25000 MPA.S); Glycerin; Propylene Glycol; Methylisothiazolinone; Trolamine; Dibasic Calcium Phosphate Dihydrate; Water; Sorbitol; Sodium Lauryl Sulfate; Sodium Pyrophosphate; Saccharin Sodium

Univ of Vermont Medical Center Amenity Kit

Colgate® Anticavity Toothpaste

Drug Facts

Active ingredient

Sodium monofluorophosphate 0.76% (0.15% w/v fluoride ion)

Purpose

Anticavity

Use

helps protect against cavities

Warnings

KEEP OUT OF REACH OF CHILDREN

Keep out of the reach of children under 6 years of age.

If more than used for brushing is accidentally swallowed, get medical help or contact a Poison Control Center right away.

Directions

adults and children 2 years of age and older | brush teeth thoroughly, preferably after each meal or at least twice a day, or as directed by a dentist or physician
children 2 to 6 years | use only a pea sized amount and supervise child's brushing and rinsing (to minimize swallowing)
children under 2 years | ask a dentist or physician

Inactive ingredients

dicalcium phosphate dihydrate, water, sorbitol, sodium lauryl sulfate, flavor, cellulose gum, tetrasodium pyrophosphate, sodium saccharin

Questions or comments?

Call toll-free 1-800-468-6502

Manufactured by:
COLGATE-PALMOLIVE (THAILAND) Limited, Chonburi 20000, Thailand.

Instant Hand Antiseptic

Drug Facts

Active Ingredient

Benzalkonium Chloride 0.095%

Propose

Antiseptic

Uses

To help reduce bacteria on hands.

Warnings

For external use only.

When using this product avoid contact with eyes and lips. If contact occurs, rinse with water.

Stop use and ask a doctor if irritation or redness develops.

Keep out of reach of children. If swallowed, get medical help or contact a Poison Control Center immediately.

Directions

Rub dime sized amount between hands until dry.

Children under 6 years of age should be supervised when using this product.

Inactive Ingredients

Glycerin, Methylisothiazolinone, Propylene Glycol, Polyquaternium-37, Triethanolamine, Water

Distributed by:
ASP Global, LLC
7800 Third Flag Parkway,
Austell, GA 30168, USA

PRINCIPAL DISPLAY PANEL - 10 g Tube Label

P1505037

Colgate®
Anticavity Toothpaste

Cavity
Protection

NET WT 10g

7
OTHER

PRINCIPAL DISPLAY PANEL - 53 mL Bottle Label

ASP
MEDICAL

Instant Hand Antiseptic
Alcohol & Fragrance Free

1.9 FL OZ / 53 mL

Distributed by:
ASP Global, LLC
7800 Third Flag Parkway,
Austell, GA 30168, USA

Rev 02

PRINCIPAL DISPLAY PANEL - Kit Label

We strive to provide a quiet environment for you
to rest in during your stay. This Welcome Packet
contains some items that are helpful in reducing
hospital noise.

The best healing happens in a quiet environment.

You can help by:

- Using a headset when watching TV
- Keeping cell phones on vibrate
- Speaking softly
- Asking family and friends to visit two at a time

We are honored to care for you.

Contents/Origins:
1.9 fl. oz. Alcohol and Fragrance Free Hand Sanitizer,
0.15 oz. net wt. Lip Balm,
Toothbrush, Sleep Mask, Ear Plugs, Notebook, Pen and
Kit Case: Made in China
Toothpaste: Made in Thailand

Lot #: XMMDDFC
Exp: YYYY-MM-DD

Distributed by:
ASP Global, LLC
7800 Third Flag Parkway, Austell, GA 30168

REV 01

THE
University of Vermont
MEDICAL CENTER

Item #: UNVMC01
Description: AMENITY KIT, UVMC,
GREEN, ZIPPERED
PO #:
Lot #: XMMDDFC
Exp: YYYY-MM-DD
Qty: 30 KIT/CS
Carton #: XXX of XXXX
Net Wt.: XX KG
Gross Wt.: XX KG
Cubic Dimensions: 57.0 x 17.0 x 27.0 CM
Assembled in China

Components Made in China:

- Alcohol and Fragrance Free Hand Sanitizer
- Lip Balm
- Toothbrush
- Sleep Mask
- Ear Plugs
- Notebook
- Pen
- Kit Case

Component Made in Thailand:

- Toothpaste

THE
University of Vermont
MEDICAL CENTER